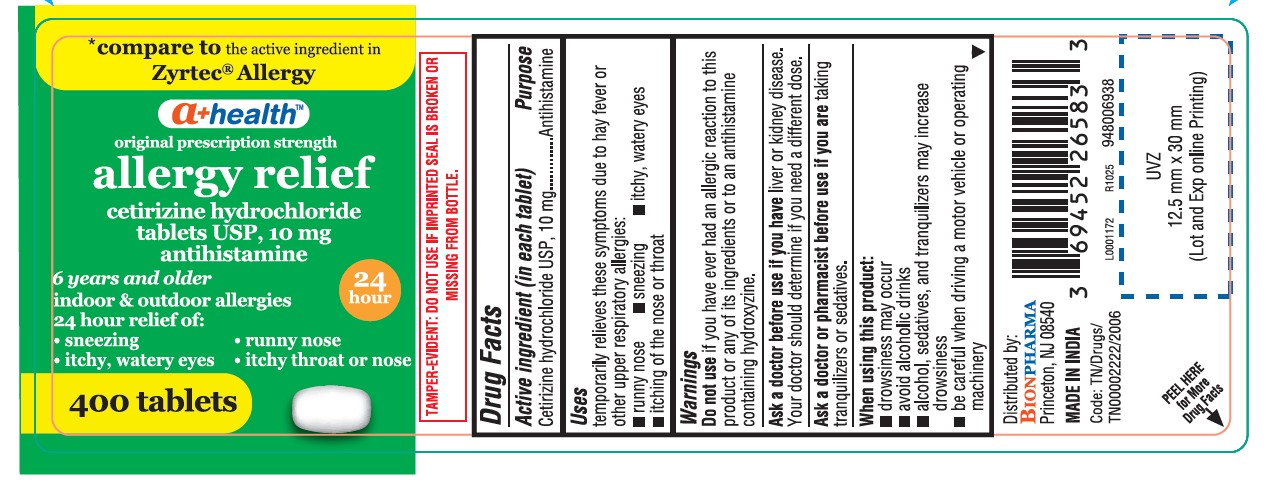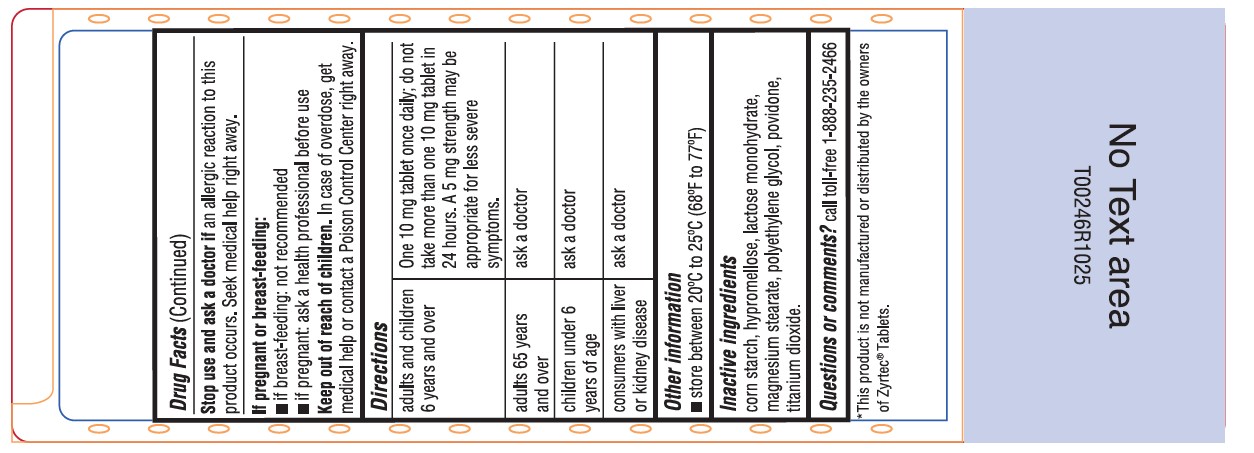 DRUG LABEL: CETIRIZINE HYDROCHLORIDE
NDC: 69452-465 | Form: TABLET, FILM COATED
Manufacturer: Bionpharma Inc.
Category: otc | Type: HUMAN OTC DRUG LABEL
Date: 20251208

ACTIVE INGREDIENTS: CETIRIZINE HYDROCHLORIDE 10 mg/1 1
INACTIVE INGREDIENTS: STARCH, CORN; LACTOSE MONOHYDRATE; POVIDONE K29/32; MAGNESIUM STEARATE; HYPROMELLOSE 2910 (5 MPA.S); TITANIUM DIOXIDE; POLYETHYLENE GLYCOL 400

Active ingredient (in each tablet)

Cetirizine Hydrochloride USP, 10 mg

Purpose

Antihistamine

Uses

temporarily relieves these symptoms due to hay fever or other upper respiratory allergies:

- runny nose
- sneezing
- itchy, watery eyes
- itching of the nose or throat

Warnings

DO NOT USE

Do not useif you have ever had an allergic reaction to this product or any of its ingredients or to an antihistamine containing hydroxyzine.

Ask a doctor before use if you haveliver or kidney disease. Your doctor should determine if you need a different dose.

Ask a doctor or pharmacist before use if you aretaking tranquilizers or sedatives.

When using this product

- drowsiness may occur
- avoid alcoholic drinks
- alcohol, sedatives, and tranquilizers may increase drowsiness
- be careful when driving a motor vehicle or operating machinery.

Stop use and ask a doctor ifan allergic reaction to this product occurs. Seek medical help right away.

If pregnant or breast-feeding:

if breast-feeding: not recommended

if pregnant: ask a health professional before use.

Keep out of reach of children.In case of overdose, get medical help or contact a Poison Control Center right away.

Directions

adults and children 6 years and over | one 10 mg tablet once daily; do not take more than one 10 mg tablet in 24 hours. A 5 mg product may be appropriate for less severe symptoms.
adults 65 years and over | ask a doctor
children under 6 years of age | ask a doctor
consumers with liver or kidney disease | ask a doctor

Other information

store between 20° to 25°C (68° to 77°F).

Inactive ingredients

corn starch, hypromellose, lactose monohydrate, magnesium stearate, polyethylene glycol, povidone, titanium dioxide

Questions or comments?

call toll-free 1-888-235-2466

This product is not manufactured or distributed by the owners of Zyrtec®Tablets.

Distributed by:

BIONPHARMA

Princeton, NJ 08540

MADE IN INDIA
Code: TN/Drugs/TN00002222/2006

L0001172

R1025

948006938

PACKAGE LABEL.PRINCIPAL DISPLAY PANEL

'compare to the active ingredient in Zyrtec® Allergy

a+healthTM

original prescription strength

allergy relief

cetirizine HCl tablets USP, 10 mg

antihistamine

6 years and older

indoor & outdoor allergies

24 hour relief of:

- sneezing
- runny nose
- itchy, watery eyes
- itchy, throat or nose

400 tablets